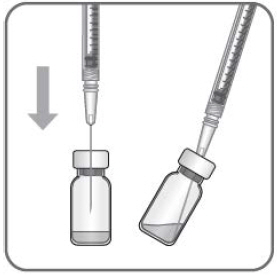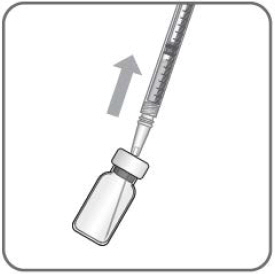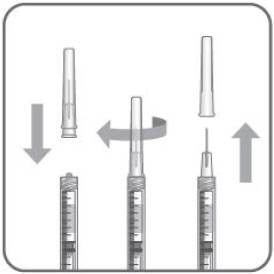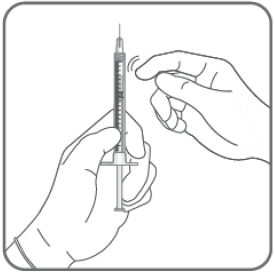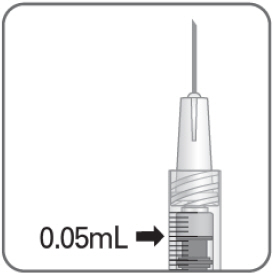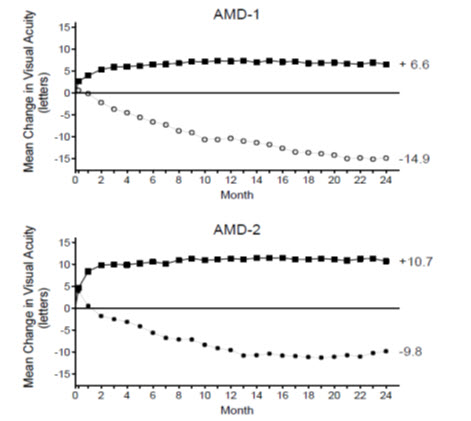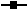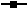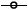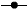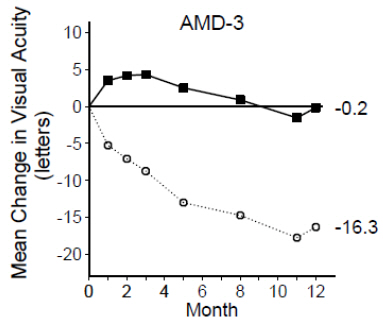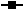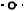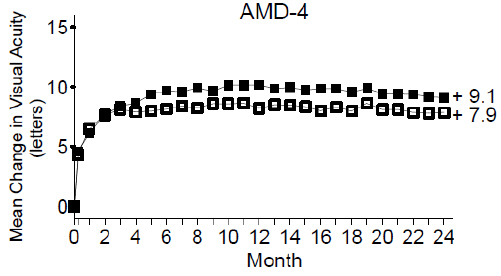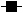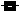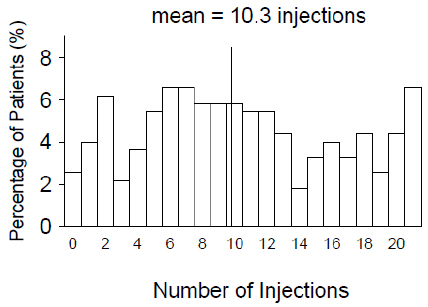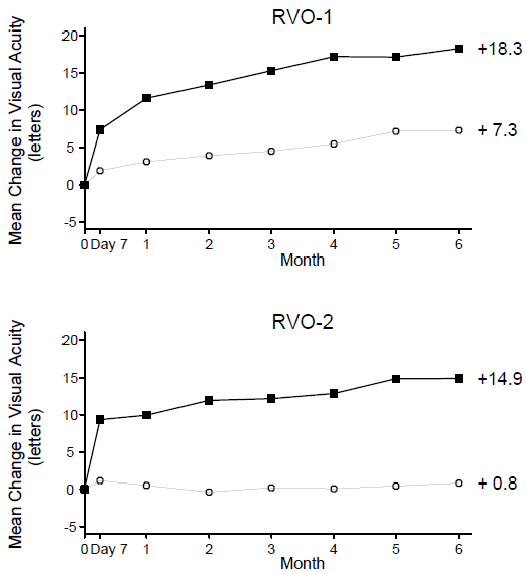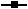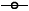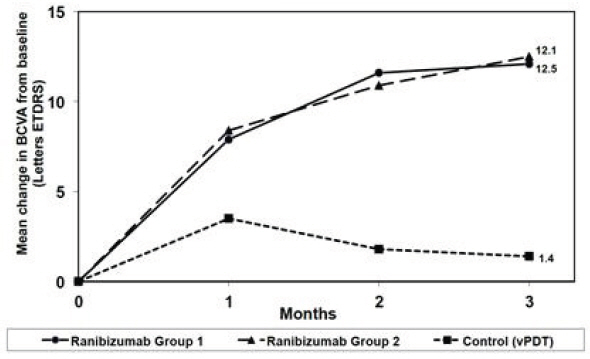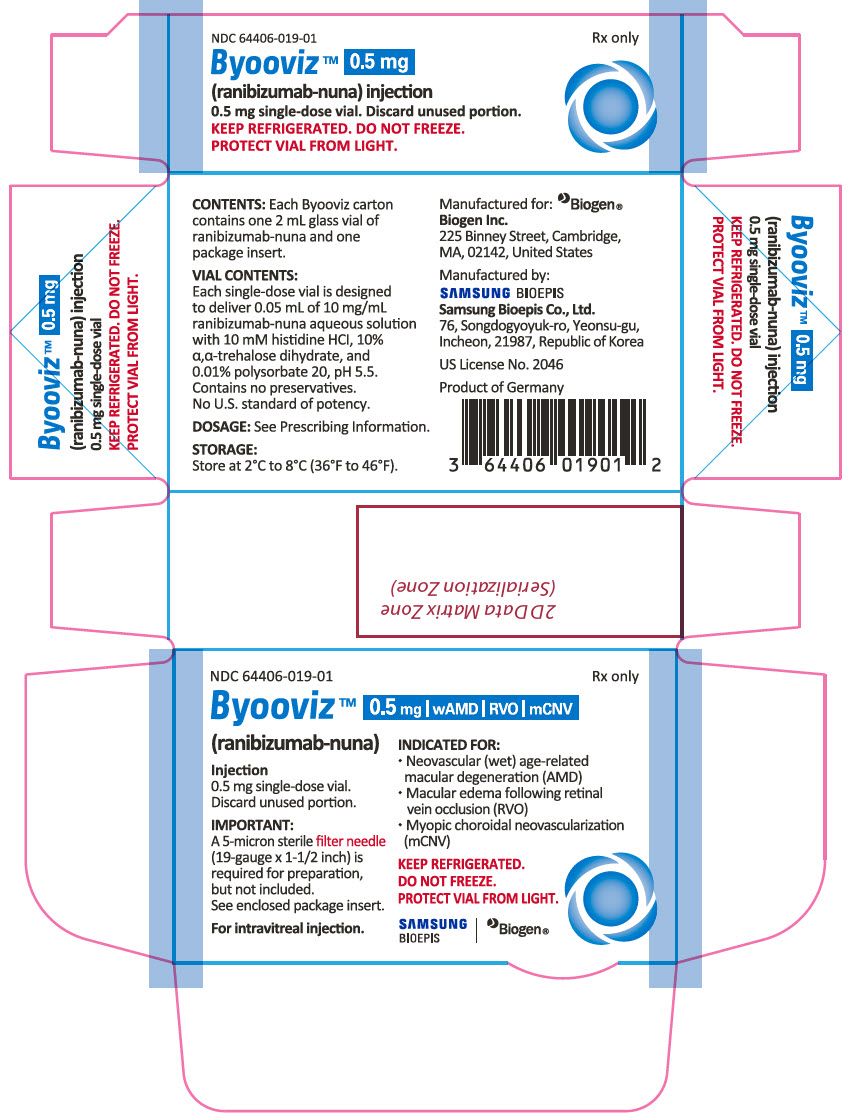 DRUG LABEL: Byooviz
NDC: 64406-019 | Form: INJECTION, SOLUTION
Manufacturer: BIOGEN INC.
Category: prescription | Type: HUMAN PRESCRIPTION DRUG LABEL
Date: 20251201

ACTIVE INGREDIENTS: RANIBIZUMAB 10 mg/1 mL
INACTIVE INGREDIENTS: HISTIDINE MONOHYDROCHLORIDE; HISTIDINE; TREHALOSE DIHYDRATE; POLYSORBATE 20; WATER

HIGHLIGHTS OF PRESCRIBING INFORMATION

These highlights do not include all the information needed to use BYOOVIZ safely and effectively. See full prescribing information for BYOOVIZ.
BYOOVIZ ® (ranibizumab-nuna) injection, for intravitreal use
Initial U.S. Approval: 2021
BYOOVIZ (ranibizumab-nuna) is biosimilar^1 to LUCENTIS (ranibizumab injection)
^1 - Biosimilar means that the biological product is approved based on data demonstrating that it is highly similar to an FDA-approved biological product, known as a reference product, and that there are no clinically meaningful differences between the biosimilar product and the reference product. Biosimilarity of BYOOVIZ has been demonstrated for the condition(s) of use (e.g., indication(s), dosing regimen(s)), strength(s), dosage form(s), and route(s) of administration described in its Full Prescribing Information.

RECENT MAJOR CHANGES

Warnings and Precautions, Retinal Vasculitis with or without Occlusion (5.4) | 8/2025

1 INDICATIONS AND USAGE

BYOOVIZ, a vascular endothelial growth factor (VEGF) inhibitor, is indicated for the treatment of patients with:

- Neovascular (Wet) Age-Related Macular Degeneration (AMD) (1.1)
- Macular Edema Following Retinal Vein Occlusion (RVO) (1.2)
- Myopic Choroidal Neovascularization (mCNV) (1.3)

2 DOSAGE AND ADMINISTRATION

For ophthalmic intravitreal injection only (2.1)

- Neovascular (Wet) Age-Related Macular Degeneration (AMD) (2.2) :
  BYOOVIZ 0.5 mg (0.05 mL) is recommended to be administered by intravitreal injection once a month (approximately 28 days).
  - Although not as effective, patients may be treated with 3 monthly doses followed by less frequent dosing with regular assessment.
  - Although not as effective, patients may also be treated with one dose every 3 months after 4 monthly doses. Patients should be assessed regularly.
- Macular Edema Following Retinal Vein Occlusion (RVO) (2.3) :
  BYOOVIZ 0.5 mg (0.05 mL) is recommended to be administered by intravitreal injection once a month (approximately 28 days).
- Myopic Choroidal Neovascularization (mCNV) (2.4) :
  BYOOVIZ 0.5 mg (0.05 mL) is recommended to be initially administered by intravitreal injection once a month (approximately 28 days) for up to three months. Patients may be retreated if needed.

3 DOSAGE FORMS AND STRENGTHS

Single-dose glass vial designed to provide 0.05 mL for intravitreal injections: 10 mg/mL solution. (3)

4 CONTRAINDICATIONS

- Ocular or periocular infections (4.1)
- Hypersensitivity (4.2)

5 WARNINGS AND PRECAUTIONS

- Endophthalmitis and retinal detachments may occur following intravitreal injections. Patients should be monitored following the injection (5.1).
- Increases in intraocular pressure (IOP) have been noted both pre- and post-intravitreal injection (5.2).
- There is a potential risk of arterial thromboembolic events following intravitreal use of VEGF inhibitors (5.3).

6 ADVERSE REACTIONS

- The most common adverse reactions (reported more frequently in ranibizumab treated subjects than control subjects) are conjunctival hemorrhage, eye pain, vitreous floaters, and increased IOP (6.2).

To report SUSPECTED ADVERSE REACTIONS, contact Biogen Inc. at 1-877-422-8360 or FDA at 1-800-FDA-1088 or www.fda.gov/medwatch.

FULL PRESCRIBING INFORMATION

1 INDICATIONS AND USAGE

BYOOVIZ is indicated for the treatment of patients with:

2 DOSAGE AND ADMINISTRATION

2.1 General Dosing Information

FOR OPHTHALMIC INTRAVITREAL INJECTION.

Vials: A 5-micron sterile filter needle (18-gauge × 1-1/2 inch or 19-gauge × 1-1/2 inch), a 1-mL Luer lock syringe and a 30- gauge × ½ inch sterile injection needle are needed but not included.

2.2 Neovascular (Wet) Age-Related Macular Degeneration (AMD)

BYOOVIZ 0.5 mg (0.05 mL of 10 mg/mL solution) is recommended to be administered by intravitreal injection once a month (approximately 28 days).

Although not as effective, patients may be treated with 3 monthly doses followed by less frequent dosing with regular assessment. In the 9 months after three initial monthly doses, less frequent dosing with 4-5 doses on average is expected to maintain visual acuity while monthly dosing may be expected to result in an additional average 1-2 letter gain. Patients should be assessed regularly [ see Clinical Studies (14.1)].

Although not as effective, patients may also be treated with one dose every 3 months after 4 monthly doses. Compared with continued monthly dosing, dosing every 3 months over the next 9 months will lead to an approximate 5-letter (1-line) loss of visual acuity benefit, on average. Patients should be assessed regularly [ see Clinical Studies (14.1)].

2.3 Macular Edema Following Retinal Vein Occlusion (RVO)

BYOOVIZ 0.5 mg (0.05 mL of 10 mg/mL solution) is recommended to be administered by intravitreal injection once a month (approximately 28 days).

In Studies RVO-1 and RVO-2, patients received monthly injections of ranibizumab for 6 months. In spite of being guided by optical coherence tomography and visual acuity re-treatment criteria, patients who were then not treated at Month 6 experienced on average, a loss of visual acuity at Month 7, whereas patients who were treated at Month 6 did not. Patients should be treated monthly [ see Clinical Studies (14.2)].

2.4 Myopic Choroidal Neovascularization (mCNV)

BYOOVIZ 0.5 mg (0.05 mL of 10 mg/mL BYOOVIZ solution) is recommended to be initially administered by intravitreal injection once a month (approximately 28 days) for up to 3 months. Patients may be retreated if needed [ see Clinical Studies (14.3)].

2.5 Preparation for Administration

Vial:

Using aseptic technique, all of the BYOOVIZ vial contents are withdrawn through a 5-micron (19- gauge × 1-1/2 inch), sterile filter needle attached to a 1 mL syringe (not included). The filter needle should be discarded after withdrawal of the vial contents and should not be used for intravitreal injection. The filter needle should be replaced with a sterile 30-gauge × ½ inch needle for the intravitreal injection.

Use aseptic technique to carry out the following preparation steps:

1. Prepare for intravitreal injection with the following medical devices for single use (not included):
  - a 5-micron sterile filter needle (18-gauge × 1-1/2 inch or 19-gauge × 1-1/2 inch)
  - a 1 mL sterile Luer lock syringe (with marking to measure 0.05 mL)
  - a sterile injection needle (30-gauge × 1/2-inch)
2. Before withdrawal, disinfect the outer part of the rubber stopper of the vial.
3. Place a 5-micron filter needle (18-gauge × 1-1/2 inch or 19-gauge × 1-1/2 inch) onto a 1 mL Luer lock syringe using aseptic technique.
4. Push the filter needle into the center of the vial stopper until the needle touches the bottom edge of the vial.
5. Withdraw all the liquid from the vial, keeping the vial in an upright position, slightly inclined to ease complete withdrawal.
6. Ensure that the plunger rod is drawn sufficiently back when emptying the vial in order to completely empty the filter needle.
7. The filter needle should be discarded after withdrawal of the vial contents and must not be used for the intravitreal injection.
8. Attach a 30-gauge × 1/2-inch sterile injection needle firmly onto the syringe by screwing it tightly onto the Luer lock. Carefully remove the needle cap by pulling it straight off. Do not wipe the needle at any time.
9. Hold the syringe with the needle pointing up. If there are any air bubbles, gently tap the syringe with your finger until the bubbles rise to the top.
10. Hold the syringe at eye level, and carefully push the plunger rod until the plunger tip is aligned with the line that marks 0.05 mL on the syringe.

2.6 Administration

The intravitreal injection procedure should be carried out under controlled aseptic conditions, which include the use of sterile gloves, a sterile drape, and a sterile eyelid speculum (or equivalent).

Adequate anesthesia and a broad-spectrum microbicide should be given prior to the injection.

Prior to and 30 minutes following the intravitreal injection, patients should be monitored for elevation in intraocular pressure using tonometry. Monitoring may also consist of a check for perfusion of the optic nerve head immediately after the injection [ see Warnings and Precautions (5.2)]. Patients should also be monitored for and instructed to report any symptoms suggestive of endophthalmitis without delay following the injection [ see Warnings and Precautions (5.1)].

Each vial should only be used for the treatment of a single eye. If the contralateral eye requires treatment, a new vial should be used and the sterile field, syringe, gloves, drapes, eyelid speculum, filter needle (vial only), and injection needles should be changed before BYOOVIZ is administered to the other eye.

No special dosage modification is required for any of the populations that have been studied (e.g., gender, elderly).

3 DOSAGE FORMS AND STRENGTHS

Single-dose glass vial designed to provide 0.05 mL for intravitreal injection. Clear to slightly opalescent and colorless to pale yellow, 10 mg/mL solution.

4 CONTRAINDICATIONS

4.1 Ocular or Periocular Infections

BYOOVIZ is contraindicated in patients with ocular or periocular infections.

4.2 Hypersensitivity

BYOOVIZ is contraindicated in patients with known hypersensitivity to ranibizumab products or any of the excipients in BYOOVIZ. Hypersensitivity reactions may manifest as severe intraocular inflammation.

5 WARNINGS AND PRECAUTIONS

5.1 Endophthalmitis and Retinal Detachments

Intravitreal injections, including those with ranibizumab products, have been associated with endophthalmitis and retinal detachments. Proper aseptic injection technique should always be used when administering BYOOVIZ. In addition, patients should be monitored following the injection to permit early treatment should an infection occur [ see Dosage and Administration (2.5, 2.6)and Patient Counseling Information (17)].

5.2 Increases in Intraocular Pressure

Increases in intraocular pressure have been noted both pre-injection and post-injection (at 60 minutes) while being treated with ranibizumab products. Monitor intraocular pressure prior to and following intravitreal injection with BYOOVIZ and manage appropriately [ see Dosage and Administration (2.6)].

5.3 Thromboembolic Events

Although there was a low rate of arterial thromboembolic events (ATEs) observed in the ranibizumab clinical trials, there is a potential risk of ATEs following intravitreal use of VEGF inhibitors. Arterial thromboembolic events are defined as nonfatal stroke, nonfatal myocardial infarction, or vascular death (including deaths of unknown cause).

Neovascular (Wet) Age-Related Macular Degeneration

The ATE rate in the three controlled neovascular AMD studies (AMD-1, AMD-2, AMD-3) during the first year was 1.9% (17 of 874) in the combined group of patients treated with 0.3 mg or 0.5 mg ranibizumab compared with 1.1% (5 of 441) in patients from the control arms [ see Clinical Studies (14.1)]. In the second year of Studies AMD-1 and AMD-2, the ATE rate was 2.6% (19 of 721) in the combined group of ranibizumab-treated patients compared with 2.9% (10 of 344) in patients from the control arms. In Study AMD-4, the ATE rates observed in the 0.5 mg arms during the first and second year were similar to rates observed in Studies AMD-1, AMD-2, and AMD-3.

In a pooled analysis of 2-year controlled studies [AMD-1, AMD-2, and a study of ranibizumab used adjunctively with verteporfin photodynamic therapy (PDT)], the stroke rate (including both ischemic and hemorrhagic stroke) was 2.7% (13 of 484) in patients treated with 0.5 mg ranibizumab compared to 1.1% (5 of 435) in patients in the control arms [odds ratio 2.2 (95% confidence interval (0.8-7.1)].

Macular Edema Following Retinal Vein Occlusion

The ATE rate in the two controlled RVO studies during the first 6 months was 0.8% in both the ranibizumab and control arms of the studies (4 of 525 in the combined group of patients treated with 0.3 mg or 0.5 mg ranibizumab and 2 of 260 in the control arms) [ see Clinical Studies (14.2)]. The stroke rate was 0.2% (1 of 525) in the combined group of ranibizumab -treated patients compared to 0.4% (1 of 260) in the control arms.

5.4 Retinal Vasculitis with or without Occlusion

Retinal vasculitis with or without occlusion, typically in the presence of preexisting intraocular inflammation or post-treatment with other intravitreal agents, have been reported with the use of ranibizumab products. Discontinue treatment with BYOOVIZ in patients who develop these events. Patients should be instructed to report any change in vision without delay [ see Patient Counseling Information (17)].

6 ADVERSE REACTIONS

The following adverse reactions are discussed in greater detail in other sections of the label:

- Endophthalmitis and Retinal Detachments [ see Warnings and Precautions (5.1)]
- Increases in Intraocular Pressure [ see Warnings and Precautions (5.2)]
- Thromboembolic Events [ see Warnings and Precautions (5.3)]

6.1 Injection Procedure

Serious adverse reactions related to the injection procedure have occurred in < 0.1% of intravitreal injections, including endophthalmitis [ see Warnings and Precautions (5.1)], rhegmatogenous retinal detachment, and iatrogenic traumatic cataract.

6.2 Clinical Trials Experience

Because clinical trials are conducted under widely varying conditions, adverse reaction rates observed in the clinical trials of a drug cannot be directly compared to rates in the clinical trials of the same or another drug and may not reflect the rates observed in practice.

The data below reflect exposure to 0.5 mg ranibizumab in 440 patients with neovascular AMD in Studies AMD-1, AMD-2, and AMD-3; in 259 patients with macular edema following RVO.

Safety data observed in 224 patients with mCNV, as well as Studies AMD-4 and D-3, were consistent with these results. On average, the rates and types of adverse reactions in patients were not significantly affected by dosing regimen.

Ocular Reactions

Table 1 shows frequently reported ocular adverse reactions in ranibizumab-treated patients compared with the control group.

Table 1 Ocular Reactions in the AMD, and RVO Studies
Adverse Reaction | AMD 2-year |  | AMD 1-year |  | RVO 6-month
Adverse Reaction | Ranibizumab 0.5 mg | Control | Ranibizumab 0.5 mg | Control | Ranibizumab 0.5 mg | Control
Adverse Reaction | n=379 | n=379 | n=440 | n=441 | n=259 | n=260
Conjunctival hemorrhage | 74% | 60% | 64% | 50% | 48% | 37%
Eye pain | 35% | 30% | 26% | 20% | 17% | 12%
Vitreous floaters | 27% | 8% | 19% | 5% | 7% | 2%
Intraocular pressure increased | 24% | 7% | 17% | 5% | 7% | 2%
Vitreous detachment | 21% | 19% | 15% | 15% | 4% | 2%
Intraocular inflammation | 18% | 8% | 13% | 7% | 1% | 3%
Cataract | 17% | 14% | 11% | 9% | 2% | 2%
Foreign body sensation in eyes | 16% | 14% | 13% | 10% | 7% | 5%
Eye irritation | 15% | 15% | 13% | 12% | 7% | 6%
Lacrimation increased | 14% | 12% | 8% | 8% | 2% | 3%
Blepharitis | 12% | 8% | 8% | 5% | 0% | 1%
Dry eye | 12% | 7% | 7% | 7% | 3% | 3%
Visual disturbance or vision blurred | 18% | 15% | 13% | 10% | 5% | 3%
Eye pruritis | 12% | 11% | 9% | 7% | 1% | 2%
Ocular hyperemia | 11% | 8% | 7% | 4% | 5% | 3%
Retinal disorder | 10% | 7% | 8% | 4% | 2% | 1%
Maculopathy | 9% | 9% | 6% | 6% | 11% | 7%
Retinal degeneration | 8% | 6% | 5% | 3% | 1% | 0%
Ocular discomfort | 7% | 4% | 5% | 2% | 2% | 2%
Conjunctival hyperemia | 7% | 6% | 5% | 4% | 0% | 0%
Posterior capsule opacification | 7% | 4% | 2% | 2% | 0% | 1%
Injection site hemorrhage | 5% | 2% | 3% | 1% | 0% | 0%

Non-Ocular Reactions

Non-ocular adverse reactions with an incidence of ≥ 5% in patients receiving ranibizumab for AMD, and/or RVO and which occurred at a ≥ 1% higher frequency in patients treated with ranibizumab compared to control are shown in Table 2. Though less common, wound healing complications were also observed in some studies.

Table 2 Non-Ocular Reactions in the AMD, and RVO Studies
Adverse Reaction | AMD 2-year |  | AMD 1-year |  | RVO 6-month
Adverse Reaction | Ranibizumab 0.5 mg | Control | Ranibizumab 0.5 mg | Control | Ranibizumab 0.5 mg | Control
Adverse Reaction | n=379 | n=379 | n=440 | n=441 | n=259 | n=260
Nasopharyngitis | 16% | 13% | 8% | 9% | 5% | 4%
Anemia | 8% | 7% | 4% | 3% | 1% | 1%
Nausea | 9% | 6% | 5% | 5% | 1% | 2%
Cough | 9% | 8% | 5% | 4% | 1% | 2%
Constipation | 5% | 7% | 3% | 4% | 0% | 1%
Seasonal allergy | 4% | 4% | 2% | 2% | 0% | 2%
Hypercholesterolemia | 5% | 5% | 3% | 2% | 1% | 1%
Influenza | 7% | 5% | 3% | 2% | 3% | 2%
Renal failure | 1% | 1% | 0% | 0% | 0% | 0%
Upper respiratory tract infection | 9% | 8% | 5% | 5% | 2% | 2%
Gastroesophageal reflux disease | 4% | 6% | 3% | 4% | 1% | 0%
Headache | 12% | 9% | 6% | 5% | 3% | 3%
Edema peripheral | 3% | 5% | 2% | 3% | 0% | 1%
Renal failure chronic | 0% | 1% | 0% | 0% | 0% | 0%
Neuropathy peripheral | 1% | 1% | 1% | 0% | 0% | 0%
Sinusitis | 8% | 7% | 5% | 5% | 3% | 2%
Bronchitis | 11% | 9% | 6% | 5% | 0% | 2%
Atrial fibrillation | 5% | 4% | 2% | 2% | 1% | 0%
Arthralgia | 11% | 9% | 5% | 5% | 2% | 1%
Chronic obstructive pulmonary disease | 6% | 3% | 3% | 1% | 0% | 0%
Wound healing complications | 1% | 1% | 1% | 0% | 0% | 0%

6.3 Immunogenicity

The observed incidence of anti-drug antibodies is highly dependent on the sensitivity and specificity of the assay. Differences in assay methods preclude meaningful comparisons of the incidence of anti-drug antibodies in the studies described below with the incidence of anti-drug antibodies in other studies, including those of ranibizumab or of other ranibizumab products.

The pre-treatment incidence of immunoreactivity to ranibizumab was 0%-5% across treatment groups. After monthly dosing with ranibizumab for 6 to 24 months, antibodies to ranibizumab were detected in approximately 1%-9% of patients.

The clinical significance of immunoreactivity to ranibizumab products are unclear at this time. Among neovascular AMD patients with the highest levels of immunoreactivity, some were noted to have iritis or vitritis.

Intraocular inflammation was not observed in patients with RVO patients with the highest levels of immunoreactivity.

6.4 Postmarketing Experience

The following adverse reactions have been identified during post-approval use of ranibizumab products. Because these reactions are reported voluntarily from a population of uncertain size, it is not always possible to reliably estimate their frequency or establish a causal relationship to drug exposure.

- Ocular: Tear of retinal pigment epithelium among patients with neovascular AMD

7 DRUG INTERACTIONS

Drug interaction studies have not been conducted with ranibizumab products.

Ranibizumab intravitreal injection has been used adjunctively with Photodynamic Therapy (PDT). Twelve of 105 (11%) patients with neovascular AMD developed serious intraocular inflammation; in 10 of the 12 patients, this occurred when ranibizumab was administered 7 days (± 2 days) after PDT.

8 USE IN SPECIFIC POPULATIONS

8.1 Pregnancy

Risk Summary

There are no adequate and well-controlled studies of ranibizumab products administered in pregnant women.

Administration of ranibizumab to pregnant monkeys throughout the period of organogenesis resulted in a low incidence of skeletal abnormalities at intravitreal doses 13-times the predicted human exposure (based on maximal serum trough levels [Cmax]) after a single eye treatment at the recommended clinical dose. No skeletal abnormalities were observed at serum trough levels equivalent to the predicted human exposure after a single eye treatment at the recommended clinical dose [ see Animal Data].

Animal reproduction studies are not always predictive of human response, and it is not known whether ranibizumab products can cause fetal harm when administered to a pregnant woman. Based on the anti-VEGF mechanism of action for ranibizumab products [ see Clinical Pharmacology (12.1)], treatment with ranibizumab products may pose a risk to human embryofetal development.

BYOOVIZ should be given to a pregnant woman only if clearly needed.

Data

Animal Data

An embryo-fetal developmental toxicity study was performed on pregnant cynomolgus monkeys. Pregnant animals received intravitreal injections of ranibizumab every 14 days starting on Day 20 of gestation, until Day 62 at doses of 0, 0.125, and 1 mg/eye. Skeletal abnormalities including incomplete and/or irregular ossification of bones in the skull, vertebral column, and hindlimbs and shortened supernumerary ribs were seen at a low incidence in fetuses from animals treated with 1 mg/eye of ranibizumab. The 1 mg/eye dose resulted in trough serum ranibizumab levels up to 13 times higher than predicted Cmax levels with single eye treatment in humans. No skeletal abnormalities were seen at the lower dose of 0.125 mg/eye, a dose which resulted in trough exposures equivalent to single eye treatment in humans. No effect on the weight or structure of the placenta, maternal toxicity, or embryotoxicity was observed.

8.2 Lactation

Risk Summary

There are no data available on the presence of ranibizumab products in human milk, the effects of ranibizumab products on the breastfed infant or the effects of ranibizumab products on milk production/excretion.

Because many drugs are excreted in human milk, and because the potential for absorption and harm to infant growth and development exists, caution should be exercised when BYOOVIZ is administered to a nursing woman.

The developmental and health benefits of breastfeeding should be considered along with the mother's clinical need for BYOOVIZ and any potential adverse effects on the breastfed child from BYOOVIZ.

8.3 Females and Males of Reproductive Potential

Infertility

No studies on the effects of ranibizumab products on fertility have been conducted and it is not known whether ranibizumab products can affect reproduction capacity. Based on the anti-VEGF mechanism of action for ranibizumab products, treatment with ranibizumab products may pose a risk to reproductive capacity.

8.4 Pediatric Use

The safety and effectiveness of BYOOVIZ in pediatric patients have not been established.

8.5 Geriatric Use

In the clinical studies, approximately 76% (2449 of 3227) of patients randomized to treatment with ranibizumab were ≥ 65 years of age and approximately 51% (1644 of 3227) were ≥ 75 years of age [ see Clinical Studies (14)]. No notable differences in efficacy or safety were seen with increasing age in these studies. Age did not have a significant effect on systemic exposure.

10 OVERDOSAGE

More concentrated doses as high as 2 mg ranibizumab in 0.05 mL have been administered to patients. No additional unexpected adverse reactions were seen.

11 DESCRIPTION

BYOOVIZ (ranibizumab-nuna) is a recombinant humanized IgG1 kappa isotype monoclonal antibody fragment designed for intraocular use. Ranibizumab-nuna binds to and inhibits the biologic activity of human vascular endothelial growth factor A (VEGF-A). Ranibizumab-nuna, which lacks an Fc region, has a molecular weight of approximately 48 kilodaltons and is produced by an E. coli expression system in a nutrient medium containing the antibiotic tetracycline. Tetracycline is not detectable in the final product.

BYOOVIZ (ranibizumab-nuna) injection is a sterile, clear to slightly opalescent and colorless to pale yellow solution in a single-dose glass vial for intravitreal use. BYOOVIZ is supplied as a preservative-free, sterile solution in a single-dose container designed to deliver 0.05 mL of 10 mg/mL BYOOVIZ (0.5 mg dose vial) aqueous solution with 10 mM histidine HCl, 10% α,α-trehalose dihydrate, 0.01% polysorbate 20, pH 5.5.

12 CLINICAL PHARMACOLOGY

12.1 Mechanism of Action

Ranibizumab products bind to the receptor binding site of active forms of VEGF-A, including the biologically active, cleaved form of this molecule, VEGF110. VEGF-A has been shown to cause neovascularization and leakage in models of ocular angiogenesis and vascular occlusion and is thought to contribute to pathophysiology of neovascular AMD, mCNV, and macular edema following RVO. The binding of ranibizumab products to VEGF-A prevents the interaction of VEGF-A with its receptors (VEGFR1 and VEGFR2) on the surface of endothelial cells, reducing endothelial cell proliferation, vascular leakage, and new blood vessel formation.

12.2 Pharmacodynamics

Increased retinal thickness (i.e., center point thickness (CPT) or central foveal thickness (CFT)), as assessed by optical coherence tomography (OCT) is associated with neovascular AMD, mCNV, and macular edema following RVO. Leakage from choroidal neovascularization (CNV) as assessed by fluorescein angiography (FA) is associated with neovascular AMD and mCNV.

Neovascular (Wet) Age-Related Macular Degeneration

In Study AMD-3, CPT was assessed by time domain (TD)-OCT in 118 of 184 patients. TD-OCT measurements were collected at baseline, Months 1, 2, 3, 5, 8, and 12. In patients treated with ranibizumab, CPT decreased, on average, more than in the sham group from baseline through Month 12. CPT decreased by Month 1 and decreased further at Month 3, on average. In this study, CPT data did not provide information useful in influencing treatment decisions [ see Clinical Studies (14.1)].

In Study AMD-4, CFT was assessed by spectral domain (SD)-OCT in all patients; on average, CFT reductions were observed beginning at Day 7 following the first ranibizumab injection through Month 24. CFT data did not provide information capable of predicting final visual acuity results [ see Clinical Studies (14.1)].

In patients treated with ranibizumab, the area of CNV leakage, on average, decreased by Month 3 as assessed by FA. The area of CNV leakage for an individual patient was not correlated with visual acuity.

Macular Edema Following Retinal Vein Occlusion

On average, CPT reductions were observed in Studies RVO-1 and RVO-2 beginning at Day 7 following the first ranibizumab injection through Month 6. CPT was not evaluated as a means to guide treatment decisions [ see Clinical Studies (14.2)].

Myopic Choroidal Neovascularization

On average CFT reductions were observed as early as Month 1, and were greater in the ranibizumab groups compared to PDT [ see Clinical Studies (14.3)].

12.3 Pharmacokinetics

In patients with neovascular AMD, following monthly intravitreal administration of 0.5 mg ranibizumab, mean (±SD) maximum ranibizumab serum concentrations were 1.7 (± 1.1) ng/mL. These concentrations were below the concentration range of ranibizumab (11 to 27 ng/mL) that was necessary to inhibit the biological activity of VEGF-A by 50%, as measured in an in vitro cellular proliferation assay (based on human umbilical vein endothelial cells (HUVEC)). No significant change from baseline was observed in the mean plasma VEGF concentrations following three monthly 0.5 mg intravitreal injections. The maximum observed serum concentration was dose proportional over the dose range of 0.05 to 2 mg/eye. Serum ranibizumab concentrations in RVO patients were similar to those observed in neovascular AMD patients.

Based on a population pharmacokinetic analysis of patients with neovascular AMD, maximum serum concentrations are predicted to be reached at approximately 1 day after monthly intravitreal administration of ranibizumab 0.5 mg/eye. Based on the disappearance of ranibizumab from serum, the estimated average vitreous elimination half-life was approximately 9 days. Steady-state minimum concentration is predicted to be 0.22 ng/mL with a monthly dosing regimen. In humans, serum ranibizumab concentrations are predicted to be approximately 90,000-fold lower than vitreal concentrations.

In pharmacokinetic covariate analyses, 48% (520/1091) of patients had renal impairment (35% mild, 11% moderate, and 2% severe). Because the increases in plasma ranibizumab exposures in these patients are not considered clinically significant, no dosage adjustment is needed based on renal impairment status.

13 NONCLINICAL TOXICOLOGY

13.1 Carcinogenesis, Mutagenesis, Impairment of Fertility

Animal studies have not been conducted to determine the carcinogenic potential of ranibizumab products. Based on the anti-VEGF mechanism of action of ranibizumab products, treatment with ranibizumab products may pose a risk to reproductive capacity [ see Females and Males of Reproductive Potential (8.3)].

14 CLINICAL STUDIES

Unless otherwise noted, visual acuity was measured at a distance of 4 meters.

14.1 Neovascular (Wet) Age-Related Macular Degeneration (AMD)

The safety and efficacy of ranibizumab were assessed in three randomized, double-masked, sham- or active-controlled studies in patients with neovascular AMD. A total of 1323 patients (ranibizumab 879, control 444) were enrolled in the three studies.

Studies AMD-1 and AMD-2

In Study AMD-1, patients with minimally classic or occult (without classic) CNV lesions received monthly ranibizumab 0.3 mg or 0.5 mg intravitreal injections or monthly sham injections. Data are available through Month 24. Patients treated with ranibizumab in Study AMD-1 received a mean of 22 total treatments out of a possible 24 from Day 0 to Month 24.

In Study AMD-2, patients with predominantly classic CNV lesions received one of the following: 1) monthly ranibizumab 0.3 mg intravitreal injections and sham PDT; 2) monthly ranibizumab 0.5 mg intravitreal injections and sham PDT; or 3) sham intravitreal injections and active PDT. Sham PDT (or active PDT) was given with the initial ranibizumab (or sham) intravitreal injection and every 3 months thereafter if FA showed persistence or recurrence of leakage. Data are available through Month 24. Patients treated with ranibizumab in Study AMD-2 received a mean of 21 total treatments out of a possible 24 from Day 0 through Month 24.

In both studies, the primary efficacy endpoint was the proportion of patients who maintained vision, defined as losing fewer than 15 letters of visual acuity at 12 months compared with baseline. Almost all ranibizumab--treated patients (approximately 95%) maintained their visual acuity. Among ranibizumab--treated patients, 31% to 37% experienced a clinically significant improvement in vision, defined as gaining 15 or more letters at 12 months. The size of the lesion did not significantly affect the results. Detailed results are shown in Table 3, Table 4, and Figure 1 below.

Table 3 Visual Acuity Outcomes at Month 12 and Month 24 in Study AMD-1
Outcome Measure | Month | Sham n=229 | Ranibizumab 0.5 mg n=230 | Estimated Difference (95% CI) [Adjusted estimate based on the stratified model; p < 0.01]
Loss of <15 letters in visual acuity (%) | 12 | 60% | 91% | 30% (23%, 37%)
Loss of <15 letters in visual acuity (%) | 24 | 56% | 89% | 33% (26%, 41%)
Gain of ≥15 letters in visual acuity (%) | 12 | 6% | 31% | 25% (18%, 31%)
Gain of ≥15 letters in visual acuity (%) | 24 | 4% | 30% | 25% (18%, 31%)
Mean change in visual acuity (letters) (SD) | 12 | -11.0 (17.9) | +6.3 (14.1) | 17.1 (14.2, 20.0)
Mean change in visual acuity (letters) (SD) | 24 | -15.0 (19.7) | +5.5 (15.9) | 20.1 (16.9, 23.4)

Table 4 Visual Acuity Outcomes at Month 12 and Month 24 in Study AMD-2
Outcome Measure | Month | PDT n=141 | Ranibizumab 0.5 mg n=139 | Estimated Difference (95% CI) [Adjusted estimate based on the stratified model; p < 0.01]
Loss of <15 letters in visual acuity (%) | 12 | 66% | 98% | 32% (24%, 40%)
Loss of <15 letters in visual acuity (%) | 24 | 65% | 93% | 28% (19%, 37%)
Gain of ≥15 letters in visual acuity (%) | 12 | 11% | 37% | 26% (17%, 36%)
Gain of ≥15 letters in visual acuity (%) | 24 | 9% | 37% | 29% (20%, 39%)
Mean change in visual acuity (letters) (SD) | 12 | -8.5 (17.8) | +11.0 (15.8) | 19.8 (15.9, 23.7)
Mean change in visual acuity (letters) (SD) | 24 | -9.1 (18.7) | +10.9 (17.3) | 20 (16.0, 24.4)

Figure 1
Mean Change in Visual Acuity [Visual acuity was measured at a distance of 2 meters] from Baseline to Month 24 in Study AMD-1 and Study AMD-2
AMD-1 |  | AMD-2
 | Ranibizumab 0.5 mg (n=240) |  | Ranibizumab 0.5 mg (n=139)
 | Sham (n=238) |  | Verteporfin PDT (n=143)

Patients in the group treated with ranibizumab had minimal observable CNV lesion growth, on average. At Month 12, the mean change in the total area of the CNV lesion was 0.1-0.3 disc areas (DA) for ranibizumab versus 2.3-2.6 DA for the control arms. At Month 24, the mean change in the total area of the CNV lesion was 0.3-0.4 DA for ranibizumab versus 2.9-3.1 DA for the control arms.

Study AMD-3

Study AMD-3 was a randomized, double-masked, sham-controlled, 2-year study designed to assess the safety and efficacy of ranibizumab in patients with neovascular AMD (with or without a classic CNV component). Data are available through Month 12. Patients received ranibizumab 0.3 mg or 0.5 mg intravitreal injections or sham injections once a month for three consecutive doses, followed by a dose administered once every 3 months for 9 months. A total of 184 patients were enrolled in this study (ranibizumab 0.3 mg, 60; ranibizumab 0.5 mg, 61; sham, 63); 171 (93%) completed 12 months of this study. Patients treated with ranibizumab in Study AMD-3 received a mean of six total treatments out of a possible 6 from Day 0 through Month 12.

In Study AMD-3, the primary efficacy endpoint was the mean change in visual acuity at 12 months compared with baseline (see Figure 2). After an initial increase in visual acuity (following monthly dosing), on average, patients dosed once every 3 months with ranibizumab lost visual acuity, returning to baseline at Month 12. In Study AMD-3, almost all ranibizumab-treated patients (90%) lost fewer than 15 letters of visual acuity at Month 12.

Figure 2
Mean Change in Visual Acuity from Baseline to Month 12 in Study AMD-3

Ranibizumab 0.5 mg (n=61)

Sham (n=63)

Study AMD-4

Study AMD-4 was a randomized, double-masked, active treatment-controlled, two-year study designed to assess the safety and efficacy of ranibizumab 0.5 mg administered monthly or less frequently than monthly in patients with neovascular AMD. Patients randomized to the ranibizumab 0.5 mg less frequent dosing arm received three monthly doses followed by monthly assessments where patients were eligible to receive ranibizumab injections guided by pre-specified re-treatment criteria. A total of 550 patients were enrolled in the two 0.5 mg treatment groups with 467 (85%) completing through Month 24. Data are available through Month 24.

Clinical results at Month 24 remain similar to that observed at Month 12.

From Month 3 through Month 24, visual acuity decreased by 0.3 letters in the 0.5 mg less frequent dosing arm and increased by 0.7 letters in the 0.5 mg monthly arm (see Figure 3). Over this 21-month period, patients in the 0.5 mg less frequent dosing and the 0.5 mg monthly arms averaged 10.3 and 18.5 injections, respectively. The distribution of injections received in the less frequent dosing arm is shown in Figure 4.

Figure 3
Mean Change in Visual Acuity from Baseline to Month 24 in Study AMD-4

Ranibizumab 0.5 mg Monthly (n=275)

Ranibizumab 0.5 mg Less Frequent than Monthly (n=275)

Figure 4
Distribution of Injections from Month 3 to Month 24 in the Less Frequent Dosing Arm in Study AMD-4

14.2 Macular Edema Following Retinal Vein Occlusion (RVO)

The safety and efficacy of ranibizumab were assessed in two randomized, double-masked, 1-year studies in patients with macular edema following RVO. Sham controlled data are available through Month 6. Patient age ranged from 20 to 91 years, with a mean age of 67 years. A total of 789 patients (ranibizumab 0.3 mg, 266 patients; ranibizumab 0.5 mg, 261 patients; sham, 262 patients) were enrolled, with 739 (94%) patients completing through Month 6. All patients completing Month 6 were eligible to receive ranibizumab injections guided by pre-specified re-treatment criteria until the end of the studies at Month 12.

In Study RVO-1, patients with macular edema following branch or hemi-RVO, received monthly ranibizumab 0.3 mg or 0.5 mg intravitreal injections or monthly sham injections for 6 months. All patients were eligible for macular focal/grid laser treatment beginning at Month 3 of the 6-month treatment period. Macular focal/grid laser treatment was given to 26 of 131 (20%) patients treated with 0.5 mg ranibizumab and 71 of 132 (54%) patients treated with sham.

In Study RVO-2, patients with macular edema following central RVO received monthly ranibizumab 0.3 mg or 0.5 mg intravitreal injections or monthly sham injections for 6 months.

At Month 6, after monthly treatment with 0.5 mg ranibizumab, the following clinical results were observed:

Table 5 Visual Acuity Outcomes at Month 6 in Study RVO-1 and Study RVO-2
Outcome Measure | Study [RVO-1: Sham, n=131; Ranibizumab 0.5 mg, n=132 RVO-2: Sham, n=130; Ranibizumab 0.5 mg, n=130] | Sham | Ranibizumab 0.5 mg | Estimated Difference (95% CI) [Adjusted estimate based on stratified model; p < 0.01]
Gain of ≥15 letters in visual acuity (%) | RVO-1 | 29% | 61% | 31% (20%, 43%)
Gain of ≥15 letters in visual acuity (%) | RVO-2 | 17% | 48% | 30% (20%, 41%)

Figure 5
Mean Change in Visual Acuity from Baseline to Month 6 in Study RVO-1 and Study RVO-2

RVO-1:

RVO-2:

Ranibizumab 0.5 mg (n=131)

Ranibizumab 0.5 mg (n=130)

Sham (n=132)

Sham (n=130)

p < 0.01 for all time points

14.3 Myopic Choroidal Neovascularization (mCNV)

The efficacy and safety data of ranibizumab were assessed in a randomized, double-masked, active-controlled 3- month study in patients with mCNV. Patients age ranged from 18 to 87 years, with a mean age of 55 years. A total of 276 patients (222 patients in the ranibizumab treated Groups I and II; 55 patients in the active control PDT group) were enrolled. Patients randomized to the ranibizumab groups received injections guided by pre- specified re-treatment criteria. The retreatment criteria in Group I were vision stability guided, with the Best Corrected Visual Acuity (BCVA) at the current visit being assessed for changes compared with the two preceding monthly BCVA values. The retreatment criteria in Group II were disease activity guided, based on BCVA decrease from the previous visit that was attributable to intra- or sub-retinal fluid or active leakage secondary to mCNV as assessed by OCT and/or FA compared to the previous monthly visit.

Visual gains for the two ranibizumab 0.5 mg treatment arms were superior to the active control arm. The mean change in BCVA from baseline at Month 3 was: +12.1 letters for Group I, +12.5 letters for Group II and +1.4 letters for the PDT group. (Figure 6; Table 6). Efficacy was comparable between Group I and Group II.

Table 6 Mean Change in Visual Acuity and Proportion of Patients who Gained ≥15 letters from Baseline at Month 3
Study Arms | Mean change in BCVA from baseline (Letters) |  | Proportion of patients who gained ≥15 letters from baseline
Study Arms | Mean (SD) | Estimated Difference (95% CI) [Adjusted estimates based on stratified models; p < 0.01] | Percent | Estimated Difference (95% CI)
Group I | 12.1 (10.2) | 10.9 (7.6, 14.3) | 37.1 | 22.6 (9.5, 35.7)
Group II | 12.5 (8.8) | 11.4 (8.3, 14.5) | 40.5 | 26.0 (13.1, 38.9)
Control (PDT) | 1.4 (12.2) |  | 14.5

Figure 6
Mean Change in Visual Acuity from Baseline to Month 3 in mCNV Study

The proportion of patients who gained ≥15 letters (ETDRS) by Month 3 was 37.1% and 40.5% for ranibizumab Groups I and II, respectively and 14.5% for the PDT group. The mean number of injections between baseline and Month 3 was 2.5 and 1.8 for Groups I and II, respectively. 41% of patients received 1, 2 or 3 injections between baseline and Month 3 with no injections afterwards.

16 HOW SUPPLIED/STORAGE AND HANDLING

Each BYOOVIZ 0.5 mg carton (NDC 64406-019-01) contains a single-dose, 2-mL glass vial designed to deliver 0.05 mL of 10 mg/mL ranibizumab-nuna solution that is clear to slightly opalescent and colorless to pale yellow.

EACH CARTON IS FOR SINGLE-EYE USE ONLY.

STORAGE AND HANDLING

BYOOVIZ should be refrigerated at 2°C to 8°C (36°F to 46°F). DO NOT FREEZE. Do not use beyond the date stamped on the label. Protect BYOOVIZ vials from light and store in the original carton until time of use.

Prior to use, the unopened vial can be stored at temperatures up to 86°F (30°C) for up to 72 hours.

17 PATIENT COUNSELING INFORMATION

Advise patients that in the days following BYOOVIZ administration, patients are at risk of developing endophthalmitis and retinal vasculitis with or without occlusion. If the eye becomes red, sensitive to light, painful, or develops a change in vision, advise the patient to seek immediate care from an ophthalmologist [ see Warnings and Precautions (5.1, 5.4)].

BYOOVIZ (ranibizumab-nuna)

Manufactured by:
Samsung Bioepis Co., Ltd.
76, Songdogyoyuk-ro,
Yeonsu-gu, Incheon, 21987
Republic of Korea
US License No. 2046

Manufactured for:
Biogen Inc.
225 Binney Street, Cambridge
MA, 02142
United States

BYOOVIZ is a trademark of Biogen MA Inc.

PRINCIPAL DISPLAY PANEL - 0.5 mg Vial Carton

NDC 64406-019-01

Rx only

Byooviz™ 0.5mg wAMD RVO mCNO

(ranibizumab-nuna)

Injection

0.5 mg single-dose vial.

Discard unused portion.

IMPORTANT:

A 5-micron sterile ﬁlter needle(19-gauge x 1-1/2 inch) is required for preparation, but not included.

See enclosed package insert.

For intravitreal injection.

INDICATED FOR:

Neovascular (wet) age-related macular degeneration (AMD)

Macular edema following retinal vein occlusion (RVO)

Myopic choroidal neovascularization (mCNV)

KEEP REFRIGERATED.

DO NOT FREEZE.

PROTECT VIAL FROM LIGHT.

SAMSUNG BIOEPIS, Biogen®